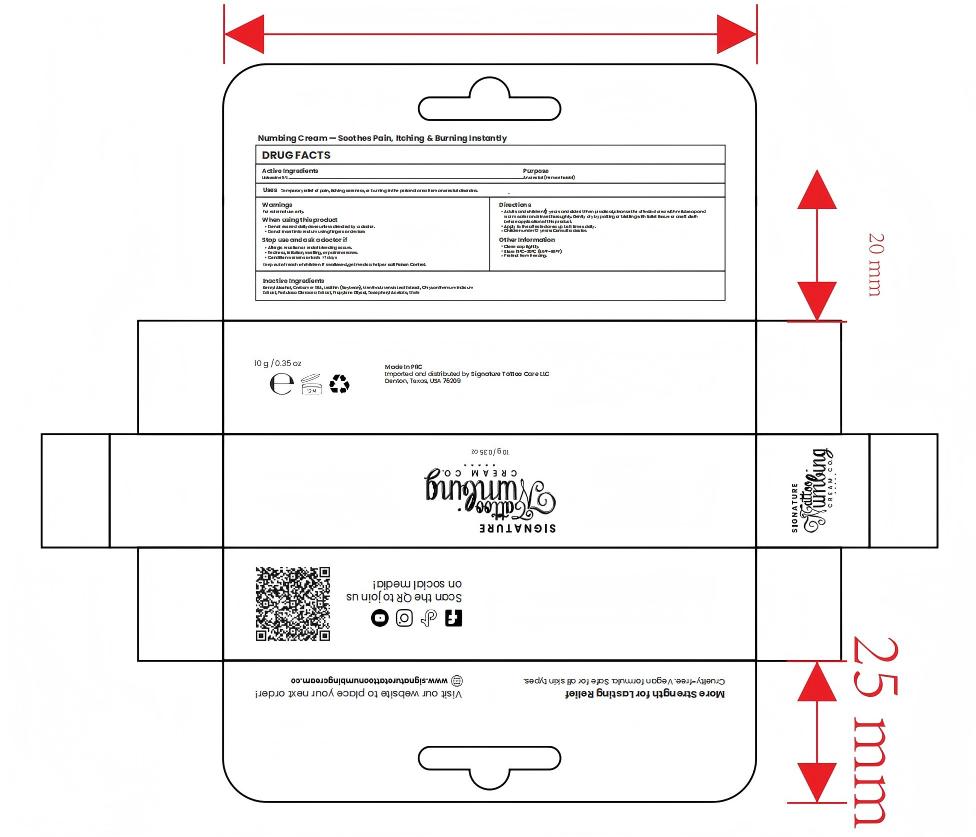 DRUG LABEL: Signature numbing cream
NDC: 84019-039 | Form: CREAM
Manufacturer: Shengnan (Guangzhou) Cosmetics Co., LTD
Category: otc | Type: HUMAN OTC DRUG LABEL
Date: 20260108

ACTIVE INGREDIENTS: LIDOCAINE 50 mg/1 g
INACTIVE INGREDIENTS: CARBOMER 934; LECITHIN, SOYBEAN; WATER; BENZYL ALCOHOL

Signature numbing cream 10g/0.35 oz

WARNINGS

For external use only

PURPOSE

Temporary relief of pain, itching, soreness, or burning in the perianal area from anorectal disorders.

STOP USE

Allergic reaction or rectal bleeding occurs.Redness,irritation, swelling, or pain increases.Condition worsens or lasts >7 days

ACTIVE INGREDIENT

5% Lidocaine

WHEN USING

Wash the area with soap and water.

INACTIVE INGREDIENT

Benzyl Alcohol, Carbomer 934, Lecithin (Soybean), Mentha Arvensis Leaf Extract, Chrysanthemum Indicum
Extract, Portulaca Oleracea Extract, Propylene Glycol, Tocopheryl Acetate, Water

DOSAGE AND ADMINISTRATION

Apply 1-3 times a week

INDICATIONS AND USAGE

Adults and children 12 years and older: When practical, cleanse the affected area with mild soap andwarm water and rinse thoroughly. Gently dry by patting or blotting with toilet tissue or a soft clothbefore application of this product.Apply to the affected area up to 6 times daily.Children under 12 years: Consult a doctor.

KEEP OUT OF CHILDREN